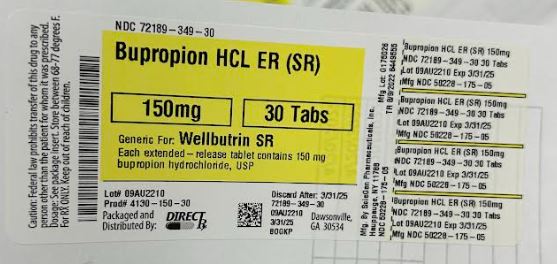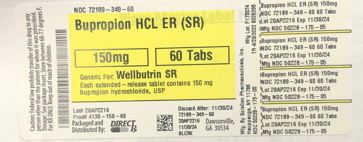 DRUG LABEL: BUPROPION HYDROCHLORIDE   SR
NDC: 72189-349 | Form: TABLET, FILM COATED, EXTENDED RELEASE
Manufacturer: DirectRx
Category: prescription | Type: HUMAN PRESCRIPTION DRUG LABEL
Date: 20250122

ACTIVE INGREDIENTS: BUPROPION HYDROCHLORIDE 150 mg/1 1
INACTIVE INGREDIENTS: TITANIUM DIOXIDE; FD&C RED NO. 40; ACACIA; FD&C BLUE NO. 2; DEXTROSE, UNSPECIFIED FORM; PROPYLENE GLYCOL; SILICON DIOXIDE; MAGNESIUM STEARATE; HYPROMELLOSE, UNSPECIFIED; POLYETHYLENE GLYCOL, UNSPECIFIED; POLYSORBATE 80; COPOVIDONE K25-31; CYSTEINE HYDROCHLORIDE; MICROCRYSTALLINE CELLULOSE; ALCOHOL

BUPROPION HCL ER (SR)

INDICATIONS AND USAGE

Bupropion hydrochloride extended-release tablets (SR) is indicated for the treatment of major depressive disorder (MDD), as defined by the Diagnostic and Statistical Manual (DSM).

The efficacy of bupropion in the treatment of a major depressive episode was established in two 4-week controlled inpatient trials and one 6-week controlled outpatient trial of adult subjects with MDD [see Clinical Studies (14)] .

The efficacy of bupropion hydrochloride extended-release tablets (SR) in maintaining an antidepressant response for up to 44 weeks following 8 weeks of acute treatment was demonstrated in a placebo-controlled trial [see Clinical Studies (14)] .

DOSAGE AND ADMINISTRATION

2.1 General Instructions for Use
To minimize the risk of seizure, increase the dose gradually [see Warnings and Precautions (5.3)] . Bupropion hydrochloride extended-release tablets (SR) should be swallowed whole and not crushed, divided, or chewed. Bupropion hydrochloride extended-release tablets (SR) may be taken with or without food.

The usual adult target dose for bupropion hydrochloride extended-release tablets (SR) is 300 mg/day, given as 150 mg twice daily. Initiate dosing with 150 mg/day given as a single daily dose in the morning. After 3 days of dosing, the dose may be increased to the 300-mg/day target dose, given as 150 mg twice daily. There should be an interval of at least 8 hours between successive doses. A maximum of 400 mg/day, given as 200 mg twice daily, may be considered for patients in whom no clinical improvement is noted after several weeks of treatment at 300 mg/day. To avoid high peak concentrations of bupropion and/or its metabolites, do not exceed 200 mg in any single dose.

It is generally agreed that acute episodes of depression require several months or longer of antidepressant drug treatment beyond the response in the acute episode. It is unknown whether the dose of bupropion hydrochloride extended-release tablets (SR) needed for maintenance treatment is identical to the dose that provided an initial response. Periodically reassess the need for maintenance treatment and the appropriate dose for such treatment.

2.2 Dose Adjustment in Patients with Hepatic Impairment
In patients with moderate to severe hepatic impairment (Child-Pugh score: 7 to 15), the maximum dose of bupropion hydrochloride extended-release tablets (SR) is 100 mg/day or 150 mg every other day. In patients with mild hepatic impairment (Child-Pugh score: 5 to 6), consider reducing the dose and/or frequency of dosing [see Use in Specific Populations (8.7), Clinical Pharmacology (12.3)].

2.3 Dose Adjustment in Patients with Renal Impairment
Consider reducing the dose and/or frequency of bupropion hydrochloride extended-release tablets (SR) in patients with renal impairment (Glomerular Filtration Rate less than 90 mL/min) [see Use in Specific Populations (8.6), Clinical Pharmacology (12.3)] .

2.4 Switching a Patient to or from a Monoamine Oxidase Inhibitor (MAOI) Antidepressant
At least 14 days should elapse between discontinuation of an MAOI intended to treat depression and initiation of therapy with bupropion hydrochloride extended-release tablets (SR). Conversely, at least 14 days should be allowed after stopping bupropion hydrochloride extended-release tablets (SR) before starting an MAOI antidepressant [see Contraindications (4), Drug Interactions (7.6)] .

2.5 Use of Bupropion Hydrochloride Extended-Release Tablets (SR) with Reversible MAOIs Such as Linezolid or Methylene Blue
Do not start bupropion hydrochloride extended-release tablets (SR) in a patient who is being treated with a reversible MAOI such as linezolid or intravenous methylene blue. Drug interactions can increase the risk of hypertensive reactions. In a patient who requires more urgent treatment of a psychiatric condition, non-pharmacological interventions, including hospitalization, should be considered [see Contraindications (4), Drug Interactions (7.6)] .

In some cases, a patient already receiving therapy with bupropion hydrochloride extended-release tablets (SR) may require urgent treatment with linezolid or intravenous methylene blue. If acceptable alternatives to linezolid or intravenous methylene blue treatment are not available and the potential benefits of linezolid or intravenous methylene blue treatment are judged to outweigh the risks of hypertensive reactions in a particular patient, bupropion hydrochloride extended-release tablets (SR) should be stopped promptly, and linezolid or intravenous methylene blue can be administered. The patient should be monitored for 2 weeks or until 24 hours after the last dose of linezolid or intravenous methylene blue, whichever comes first. Therapy with bupropion hydrochloride extended-release tablets (SR) may be resumed 24 hours after the last dose of linezolid or intravenous methylene blue.

The risk of administering methylene blue by non-intravenous routes (such as oral tablets or by local injection) or in intravenous doses much lower than 1 mg/kg with bupropion hydrochloride extended-release tablets (SR) is unclear. The clinician should, nevertheless, be aware of the possibility of a drug interaction with such use [see Contraindications (4), Drug Interactions (7.6)] .

DOSAGE FORMS AND STRENGTHS

100 mg – blue, round, biconvex, film coated tablets, debossed with ‘SG, 174’ on one side and plain on other side.

150 mg – purple, round, biconvex, film coated tablets, debossed with ‘SG, 175’ on one side and plain on other side.

200 mg – pink, round, biconvex, film coated tablets, debossed with ‘SG, 176’ on one side and plain on other side.

CONTRAINDICATIONS

Bupropion hydrochloride extended-release tablets (SR) are contraindicated in patients with a seizure disorder.
Bupropion hydrochloride extended-release tablets (SR) are contraindicated in patients with a current or prior diagnosis of bulimia or anorexia nervosa as a higher incidence of seizures was observed in such patients treated with the immediate-release formulation of bupropion [see Warnings and Precautions (5.3)].
Bupropion hydrochloride extended-release tablets (SR) are contraindicated in patients undergoing abrupt discontinuation of alcohol, benzodiazepines, barbiturates, and antiepileptic drugs [see Warnings and Precautions (5.3), Drug Interactions (7.3)] .
The use of MAOIs (intended to treat psychiatric disorders) concomitantly with bupropion hydrochloride extended-release tablets (SR) or within 14 days of discontinuing treatment with bupropion hydrochloride extended-release tablets (SR) is contraindicated. There is an increased risk of hypertensive reactions when bupropion hydrochloride extended-release tablets (SR) are used concomitantly with MAOIs. The use of bupropion hydrochloride extended-release tablets (SR) within 14 days of discontinuing treatment with an MAOI is also contraindicated. Starting bupropion hydrochloride extended-release tablets (SR) in a patient treated with reversible MAOIs such as linezolid or intravenous methylene blue is contraindicated [see Dosage and Administration (2.4, 2.5), Warnings and Precautions (5.4), Drug Interactions (7.6)].
Bupropion hydrochloride extended-release tablets (SR) are contraindicated in patients with known hypersensitivity to bupropion or other ingredients of bupropion hydrochloride extended-release tablets (SR). Anaphylactoid/anaphylactic reactions and Stevens-Johnson syndrome have been reported [see Warnings and Precautions (5.8)].

WARNINGS AND PRECAUTIONS

5.1 Suicidal Thoughts and Behaviors in Children, Adolescents, and Young Adults
Patients with MDD, both adult and pediatric, may experience worsening of their depression and/or the emergence of suicidal ideation and behavior (suicidality) or unusual changes in behavior, whether or not they are taking antidepressant medications, and this risk may persist until significant remission occurs. Suicide is a known risk of depression and certain other psychiatric disorders, and these disorders themselves are the strongest predictors of suicide. There has been a long-standing concern that antidepressants may have a role in inducing worsening of depression and the emergence of suicidality in certain patients during the early phases of treatment.
Pooled analyses of short-term placebo-controlled trials of antidepressant drugs (selective serotonin reuptake inhibitors [SSRIs] and others) show that these drugs increase the risk of suicidal thinking and behavior (suicidality) in children, adolescents, and young adults (ages 18 to 24) with MDD and other psychiatric disorders. Short-term clinical trials did not show an increase in the risk of suicidality with antidepressants compared with placebo in adults beyond age 24; there was a reduction with antidepressants compared with placebo in adults aged 65 and older.
The pooled analyses of placebo-controlled trials in children and adolescents with MDD, obsessive compulsive disorder (OCD), or other psychiatric disorders included a total of 24 short term trials of 9 antidepressant drugs in over 4,400 subjects. The pooled analyses of placebo-controlled trials in adults with MDD or other psychiatric disorders included a total of 295 short-term trials (median duration of 2 months) of 11 antidepressant drugs in over 77,000 subjects. There was considerable variation in risk of suicidality among drugs, but a tendency toward an increase in the younger subjects for almost all drugs studied. There were differences in absolute risk of suicidality across the different indications, with the highest incidence in MDD. The risk differences (drug vs. placebo), however, were relatively stable within age strata and across indications. These risk differences (drug-placebo difference in the number of cases of suicidality per 1,000 subjects treated) are provided in TABLE 1.
Table 1. Risk Differences in the Number of Suicidality Cases by Age Group in the Pooled Placebo-Controlled Trials of Antidepressants in Pediatric and Adult Subjects
Age Range Drug-Placebo Difference in Number of Cases of Suicidality per 1,000 Subjects Treated
Increases Compared With Placebo
<18 14 additional cases
18 to 24
5 additional cases
Decreases Compared With Placebo
25 to 64
1 fewer case
≥65
6 fewer cases
No suicides occurred in any of the pediatric trials. There were suicides in the adult trials, but the number was not sufficient to reach any conclusion about drug effect on suicide.
It is unknown whether the suicidality risk extends to longer-term use, i.e., beyond several months. However, there is substantial evidence from placebo-controlled maintenance trials in adults with depression that the use of antidepressants can delay the recurrence of depression.
All patients being treated with antidepressants for any indication should be monitored appropriately and observed closely for clinical worsening, suicidality, and unusual changes in behavior, especially during the initial few months of a course of drug therapy, or at times of dose changes, either increases or decreases [see BOXED WARNING] .
The following symptoms, anxiety, agitation, panic attacks, insomnia, irritability, hostility, aggressiveness, impulsivity, akathisia (psychomotor restlessness), hypomania, and mania, have been reported in adult and pediatric patients being treated with antidepressants for major depressive disorder as well as for other indications, both psychiatric and nonpsychiatric. Although a causal link between the emergence of such symptoms and either the worsening of depression and/or the emergence of suicidal impulses has not been established, there is concern that such symptoms may represent precursors to emerging suicidality.
Consideration should be given to changing the therapeutic regimen, including possibly discontinuing the medication, in patients whose depression is persistently worse, or who are experiencing emergent suicidality or symptoms that might be precursors to worsening depression or suicidality, especially if these symptoms are severe, abrupt in onset, or were not part of the patient’s presenting symptoms.
Families and caregivers of patients being treated with antidepressants for MDD or other indications, both psychiatric and nonpsychiatric, should be alerted about the need to monitor patients for the emergence of agitation, irritability, unusual changes in behavior, and the other symptoms described above, as well as the emergence of suicidality, and to report such symptoms immediately to healthcare providers. Such monitoring should include daily observation by families and caregivers. Prescriptions for bupropion hydrochloride extended-release tablets (SR) should be written for the smallest quantity of tablets consistent with good patient management, in order to reduce the risk of overdose.
5.2 Neuropsychiatric Adverse Events and Suicide Risk in Smoking Cessation Treatment
Bupropion hydrochloride extended-release tablets (SR) is not approved for smoking cessation treatment; however, it contains the same active ingredient as the smoking cessation medication ZYBAN. Serious neuropsychiatric adverse events have been reported in patients taking bupropion for smoking cessation. These postmarketing reports have included changes in mood (including depression and mania), psychosis, hallucinations, paranoia, delusions, homicidal ideation, aggression, hostility, agitation, anxiety, and panic, as well as suicidal ideation, suicide attempt, and completed suicide [see Adverse Reactions (6.2)] . Some patients who stopped smoking may have been experiencing symptoms of nicotine withdrawal, including depressed mood. Depression, rarely including suicidal ideation, has been reported in smokers undergoing a smoking cessation attempt without medication. However, some of these adverse events occurred in patients taking bupropion who continued to smoke.
Neuropsychiatric adverse events occurred in patients without and with pre-existing psychiatric disease; some patients experienced worsening of their psychiatric illnesses. Observe patients for the occurrence of neuropsychiatric adverse events. Advise patients and caregivers that the patient should stop taking bupropion hydrochloride extended-release tablets and contact a healthcare provider immediately if agitation, depressed mood, or changes in behavior or thinking that are not typical for the patient are observed, or if the patient develops suicidal ideation or suicidal behavior. In many postmarketing cases, resolution of symptoms after discontinuation of bupropion was reported. However, the symptoms persisted in some cases; therefore, ongoing monitoring and supportive care should be provided until symptoms resolve.
5.3 Seizure
Bupropion hydrochloride extended-release tablets (SR) can cause seizure. The risk of seizure is dose-related. The dose should not exceed 400 mg per day. Increase the dose gradually. Discontinue bupropion hydrochloride extended-release tablets (SR) and do not restart treatment if the patient experiences a seizure.
The risk of seizures is also related to patient factors, clinical situations, and concomitant medications that lower the seizure threshold. Consider these risks before initiating treatment with bupropion hydrochloride extended-release tablets (SR). Bupropion hydrochloride extended-release tablets (SR) are contraindicated in patients with a seizure disorder, current or prior diagnosis of anorexia nervosa or bulimia, or undergoing abrupt discontinuation of alcohol, benzodiazepines, barbiturates, and antiepileptic drugs [see Contraindications (4), Drug Interactions (7.3)] . The following conditions can also increase the risk of seizure: severe head injury; arteriovenous malformation; CNS tumor or CNS infection; severe stroke; concomitant use of other medications that lower the seizure threshold (e.g., other bupropion products, antipsychotics, tricyclic antidepressants, theophylline, and systemic corticosteroids); metabolic disorders (e.g., hypoglycemia, hyponatremia, severe hepatic impairment, and hypoxia); use of illicit drugs (e.g., cocaine); or abuse or misuse of prescription drugs such as CNS stimulants. Additional predisposing conditions include diabetes mellitus treated with oral hypoglycemic drugs or insulin; use of anorectic drugs; and excessive use of alcohol, benzodiazepines, sedative/hypnotics, or opiates.
Incidence of Seizure with Bupropion Use:
When bupropion hydrochloride extended-release tablets (SR) are dosed up to 300 mg per day, the incidence of seizure is approximately 0.1% (1/1,000) and increases to approximately 0.4% (4/1,000) at the maximum recommended dose of 400 mg/day.
The risk of seizure can be reduced if the dose of bupropion hydrochloride extended-release tablets (SR) does not exceed 400 mg/day, given as 200 mg twice daily, and the titration rate is gradual.
5.4 Hypertension
Treatment with bupropion hydrochloride extended-release tablets (SR) can result in elevated blood pressure and hypertension. Assess blood pressure before initiating treatment with bupropion hydrochloride extended-release tablets (SR), and monitor periodically during treatment. The risk of hypertension is increased if bupropion hydrochloride extended-release tablets (SR) are used concomitantly with MAOIs or other drugs that increase dopaminergic or noradrenergic activity [see Contraindications (4)].
Data from a comparative trial of the sustained-release formulation of bupropion HCl, nicotine transdermal system (NTS), the combination of sustained-release bupropion plus NTS, and placebo as an aid to smoking cessation suggest a higher incidence of treatment-emergent hypertension in patients treated with the combination of sustained-release bupropion and NTS. In this trial, 6.1% of subjects treated with the combination of sustained-release bupropion and NTS had treatment-emergent hypertension compared with 2.5%, 1.6%, and 3.1% of subjects treated with sustained-release bupropion, NTS, and placebo, respectively. The majority of these subjects had evidence of pre-existing hypertension. Three subjects (1.2%) treated with the combination of sustained-release bupropion and NTS and 1 subject (0.4%) treated with NTS had study medication discontinued due to hypertension compared with none of the subjects treated with sustained-release bupropion or placebo. Monitoring of blood pressure is recommended in patients who receive the combination of bupropion and nicotine replacement.
In a clinical trial of bupropion immediate-release in MDD subjects with stable congestive heart failure (N = 36), bupropion was associated with an exacerbation of pre-existing hypertension in 2 subjects, leading to discontinuation of bupropion treatment. There are no controlled trials assessing the safety of bupropion in patients with a recent history of myocardial infarction or unstable cardiac disease.
5.5 Activation of Mania/Hypomania
Antidepressant treatment can precipitate a manic, mixed, or hypomanic manic episode. The risk appears to be increased in patients with bipolar disorder or who have risk factors for bipolar disorder. Prior to initiating bupropion hydrochloride extended-release tablets (SR), screen patients for a history of bipolar disorder and the presence of risk factors for bipolar disorder (e.g., family history of bipolar disorder, suicide, or depression). Bupropion hydrochloride extended-release tablets (SR) are not approved for use in treating bipolar depression.
5.6 Psychosis and Other Neuropsychiatric Reactions
Depressed patients treated with bupropion hydrochloride extended-release tablets (SR) have had a variety of neuropsychiatric signs and symptoms, including delusions, hallucinations, psychosis, concentration disturbance, paranoia, and confusion. Some of these patients had a diagnosis of bipolar disorder. In some cases, these symptoms abated upon dose reduction and/or withdrawal of treatment. Instruct patients to contact a healthcare professional if such reactions occur.
5.7 Angle-Closure Glaucoma
The pupillary dilation that occurs following use of many antidepressant drugs including bupropion hydrochloride extended-release tablets (SR) may trigger an angle-closure attack in a patient with anatomically narrow angles who does not have a patent iridectomy.
5.8 Hypersensitivity Reactions
Anaphylactoid/anaphylactic reactions have occurred during clinical trials with bupropion. Reactions have been characterized by pruritus, urticaria, angioedema, and dyspnea requiring medical treatment. In addition, there have been rare, spontaneous postmarketing reports of erythema multiforme, Stevens-Johnson syndrome, and anaphylactic shock associated with bupropion. Instruct patients to discontinue bupropion hydrochloride extended-release tablets (SR) and consult a healthcare provider if they develop an allergic or anaphylactoid/anaphylactic reaction (e.g., skin rash, pruritus, hives, chest pain, edema, and shortness of breath) during treatment.
There are reports of arthralgia, myalgia, fever with rash, and other serum sickness-like symptoms suggestive of delayed hypersensitivity.

ADVERSE REACTIONS

The following adverse reactions are discussed in greater detail in other sections of the labeling:
Suicidal thoughts and behaviors in adolescents and young adults [see BOXED WARNING, Warnings and Precautions (5.1)]
Neuropsychiatric symptoms and suicide risk in smoking cessation treatment [see Warnings and Precautions (5.2)]
Seizure [see Warnings and Precautions (5.3)]
Hypertension [see Warnings and Precautions (5.4)]
Activation of mania or hypomania [see Warnings and Precautions (5.5)]
Psychosis and other neuropsychiatric reactions [see Warnings and Precautions (5.6)]
Angle-closure glaucoma [see Warnings and Precautions (5.7)]
Hypersensitivity reactions [see Warnings and Precautions (5.8)]
6.1 Clinical Trials Experience
Because clinical trials are conducted under widely varying conditions, adverse reaction rates observed in the clinical trials of a drug cannot be directly compared with rates in the clinical trials of another drug and may not reflect the rates observed in clinical practice.
Adverse Reactions Leading to Discontinuation of Treatment
In placebo-controlled clinical trials, 4%, 9%, and 11% of the placebo, 300 mg/day, and 400 mg/day groups, respectively, discontinued treatment due to adverse reactions. The specific adverse reactions leading to discontinuation in at least 1% of the 300 mg/day or 400 mg/day groups and at a rate at least twice the placebo rate are listed in Table 2.
Table 2. Treatment Discontinuations Due to Adverse Reactions in Placebo‑Controlled Trials
Adverse Reaction
Placebo
(n = 385)
Bupropion Hydrochloride Extended-release Tablets (SR) 300 mg/day
(n = 376)
Bupropion Hydrochloride Extended-release Tablets (SR) 400 mg/day
(n = 114)
Rash
0.0%
2.4%
0.9%
Nausea
0.3%
0.8%
1.8%
Agitation
0.3%
0.3%
1.8%
Migraine
0.3%
0.0%
1.8%
Commonly Observed Adverse Reactions
Adverse reactions from Table 3 occurring in at least 5% of subjects treated with bupropion hydrochloride extended-release tablets (SR) and at a rate at least twice the placebo rate are listed below for the 300 mg/day and 400 mg/day dose groups.
Bupropion hydrochloride extended-release tablets (SR) 300 mg/day: Anorexia, dry mouth, rash, sweating, tinnitus, and tremor.
Bupropion hydrochloride extended-release tablets (SR) 400 mg/day: Abdominal pain, agitation, anxiety, dizziness, dry mouth, insomnia, myalgia, nausea, palpitation, pharyngitis, sweating, tinnitus, and urinary frequency.
Adverse reactions reported in placebo-controlled trials are presented in TABLE 3. Reported adverse reactions were classified using a COSTART-based Dictionary.
Table 3. Adverse Reactions Reported by at Least 1% of Subjects and at a Greater Frequency than Placebo in Controlled Clinical Trials
Body System/
Adverse Reaction
Bupropion Hydrochloride Extended-release Tablets (SR) 300 mg/day
(n = 376)
Bupropion Hydrochloride Extended-release Tablets (SR) 400 mg/day
(n = 114)
Placebo
(n = 385)
Body (General)
Headache 26% 25% 23%
Infection 8% 9% 6%
Abdominal pain 3% 9% 2%
Asthenia 2% 4% 2%
Chest pain 3% 4% 1%
Pain 2% 3% 2%
Fever 1% 2% —
Cardiovascular
Palpitation 2% 6% 2%
Flushing 1% 4% —
Migraine 1% 4% 1%
Hot flashes 1% 3% 1%
Digestive
Dry mouth 17% 24% 7%
Nausea 13% 18% 8%
Constipation 10% 5% 7%
Diarrhea 5% 7% 6%
Anorexia 5% 3% 2%
Vomiting 4% 2% 2%
Dysphagia 0% 2% 0%
Musculoskeletal
Myalgia 2% 6% 3%
Arthralgia 1% 4% 1%
Arthritis 0% 2% 0%
Twitch 1% 2% —
Nervous system
Insomnia 11% 16% 6%
Dizziness 7% 11% 5%
Agitation 3% 9% 2%
Anxiety 5% 6% 3%
Tremor 6% 3% 1%
Nervousness 5% 3% 3%
Somnolence 2% 3% 2%
Irritability 3% 2% 2%
Memory decreased — 3% 1%
Paresthesia 1% 2% 1%
Central nervous system stimulation 2% 1% 1%
Respiratory
Pharyngitis 3% 11% 2%
Sinusitis 3% 1% 2%
Increased cough 1% 2% 1%
Skin
Sweating 6% 5% 2%
Rash 5% 4% 1%
Pruritus 2% 4% 2%
Urticaria 2% 1% 0%
Special senses
Tinnitus 6% 6% 2%
Taste perversion 2% 4% —
Blurred vision or diplopia 3% 2% 2%
Urogenital
Urinary frequency 2% 5% 2%
Urinary urgency — 2% 0%
Vaginal hemorrhage a 0% 2% —
Urinary tract infection 1% 0% —
aIncidence based on the number of female subjects.
— Hyphen denotes adverse events occurring in greater than 0 but less than 0.5% of subjects.
Other Adverse Reactions Observed During the Clinical Development of Bupropion
In addition to the adverse reactions noted above, the following adverse reactions have been reported in clinical trials with the sustained-release formulation of bupropion in depressed subjects and in nondepressed smokers, as well as in clinical trials with the immediate release formulation of bupropion.
Adverse reaction frequencies represent the proportion of subjects who experienced a treatment-emergent adverse reaction on at least one occasion in placebo-controlled trials for depression (n = 987) or smoking cessation (n = 1,013), or subjects who experienced an adverse reaction requiring discontinuation of treatment in an open-label surveillance trial with bupropion hydrochloride extended-release tablets (SR) (n = 3,100). All treatment-emergent adverse reactions are included except those listed in Table 3, those listed in other safety-related sections of the prescribing information, those subsumed under COSTART terms that are either overly general or excessively specific so as to be uninformative, those not reasonably associated with the use of the drug, and those that were not serious and occurred in fewer than 2 subjects.
Adverse reactions are further categorized by body system and listed in order of decreasing frequency according to the following definitions of frequency: Frequent adverse reactions are defined as those occurring in at least 1/100 subjects. Infrequent adverse reactions are those occurring in 1/100 to 1/1,000 subjects, while rare events are those occurring in less than 1/1,000 subjects.
Body (General): Infrequent were chills, facial edema, and photosensitivity. Rare was malaise.
Cardiovascular: Infrequent were postural hypotension, stroke, tachycardia, and vasodilation. Rare were syncope and myocardial infarction.
Digestive: Infrequent were abnormal liver function, bruxism, gastric reflux, gingivitis, increased salivation, jaundice, mouth ulcers, stomatitis, and thirst. Rare was edema of tongue.
Hemic and Lymphatic: Infrequent was ecchymosis.
Metabolic and Nutritional: Infrequent were edema and peripheral edema.
Musculoskeletal: Infrequent were leg cramps.
Nervous System: Infrequent were abnormal coordination, decreased libido, depersonalization, dysphoria, emotional lability, hostility, hyperkinesia, hypertonia, hypesthesia, suicidal ideation, and vertigo. Rare were amnesia, ataxia, derealization, and hypomania.
Respiratory: Rare was bronchospasm.
Special Senses: Infrequent were accommodation abnormality and dry eye.
Urogenital: Infrequent were impotence, polyuria, and prostate disorder.
Changes in Body Weight
In placebo-controlled trials, subjects experienced weight gain or weight loss as shown in TABLE 4.
Table 4. Incidence of Weight Gain and Weight Loss (≥5 lbs) in Placebo-Controlled Trials
Weight Change Bupropion Hydrochloride Extended-release Tablets (SR) 300 mg/day
(n = 339)
Bupropion Hydrochloride Extended-release Tablets (SR) 400 mg/day
(n = 112)
Placebo
(n = 347)
Gained >5 lbs 3% 2% 4%
Lost >5 lbs 14% 19% 6%
In clinical trials conducted with the immediate release formulation of bupropion, 35% of subjects receiving tricyclic antidepressants gained weight, compared with 9% of subjects treated with the immediate-release formulation of bupropion. If weight loss is a major presenting sign of a patient’s depressive illness, the anorectic and/or weight reducing potential of bupropion hydrochloride extended-release tablets (SR) should be considered.
6.2 Postmarketing Experience
The following adverse reactions have been identified during post-approval use of bupropion hydrochloride extended-release tablets (SR) and are not described elsewhere in the label. Because these reactions are reported voluntarily from a population of uncertain size, it is not always possible to reliably estimate their frequency or establish a causal relationship to drug exposure.
Body (General)
Arthralgia, myalgia, and fever with rash and other symptoms suggestive of delayed hypersensitivity. These symptoms may resemble serum sickness [see Warnings and Precautions (5.8)].
Cardiovascular
Complete atrioventricular block, extrasystoles, hypotension, hypertension (in some cases severe), phlebitis, and pulmonary embolism.
Digestive
Colitis, esophagitis, gastrointestinal hemorrhage, gum hemorrhage, hepatitis, intestinal perforation, pancreatitis, and stomach ulcer.
Endocrine
Hyperglycemia, hypoglycemia, hyponatremia, and syndrome of inappropriate antidiuretic hormone secretion.
Hemic and Lymphatic
Anemia, leukocytosis, leukopenia, lymphadenopathy, pancytopenia, and thrombocytopenia. Altered PT and/or INR, infrequently associated with hemorrhagic or thrombotic complications, were observed when bupropion was coadministered with warfarin.
Metabolic and Nutritional
Glycosuria.
Musculoskeletal
Muscle rigidity/fever/rhabdomyolysis and muscle weakness.
Nervous System
Abnormal electroencephalogram (EEG), aggression, akinesia, aphasia, coma, completed suicide, delirium, delusions, dysarthria, euphoria, extrapyramidal syndrome (dyskinesia, dystonia, hypokinesia, parkinsonism), hallucinations, increased libido, manic reaction, neuralgia, neuropathy, paranoid ideation, restlessness, suicide attempt, and unmasking tardive dyskinesia.
Respiratory
Pneumonia.
Skin
Alopecia, angioedema, exfoliative dermatitis, hirsutism, and Stevens-Johnson syndrome.
Special Senses
Deafness, increased intraocular pressure, and mydriasis.
Urogenital
Abnormal ejaculation, cystitis, dyspareunia, dysuria, gynecomastia, menopause, painful erection, salpingitis, urinary incontinence, urinary retention, and vaginitis.

OVERDOSAGE

10.1 Human Overdose Experience
Overdoses of up to 30 grams or more of bupropion have been reported. Seizure was reported in approximately one-third of all cases. Other serious reactions reported with overdoses of bupropion alone included hallucinations, loss of consciousness, mental status changes, sinus tachycardia, ECG changes such as conduction disturbances (including QRS prolongation) or arrhythmias, clonus, myoclonus, and hyperreflexia. Fever, muscle rigidity, rhabdomyolysis, hypotension, stupor, coma, and respiratory failure have been reported mainly when bupropion was part of multiple drug overdoses.

Although most patients recovered without sequelae, deaths associated with overdoses of bupropion alone have been reported in patients ingesting large doses of the drug. Multiple uncontrolled seizures, bradycardia, cardiac failure, and cardiac arrest prior to death were reported in these patients.

10.2 Overdosage Management
Consult a Certified Poison Control Center for up-to-date guidance and advice. Telephone numbers for certified poison control centers are listed in the Physician’s Desk Reference (PDR). Call 1-800-222-1222 or refer to www.poison.org.

There are no known antidotes for bupropion. In case of an overdose, provide supportive care, including close medical supervision and monitoring. Consider the possibility of multiple drug overdose. Ensure an adequate airway, oxygenation, and ventilation. Monitor cardiac rhythm and vital signs. Induction of emesis is not recommended.

DESCRIPTION

Bupropion hydrochloride extended-release tablets, USP (SR), an antidepressant of the aminoketone class, is chemically unrelated to tricyclic, tetracyclic, selective serotonin re-uptake inhibitor, or other known antidepressant agents. Its structure closely resembles that of diethylpropion; it is related to phenylethylamines. It is designated as (±)-1-(3-chlorophenyl)-2-[(1,1dimethylethyl)amino]-1-propanone hydrochloride. The molecular weight is 276.2. The molecular formula is C 13H 18ClNO•HCl. Bupropion hydrochloride powder is white, powder, soluble in 0.1N HCl, alcohol 96% and in water. It has a bitter taste and produces the sensation of local anesthesia on the oral mucosa. The structural formula is:

Chemical Structure
Bupropion hydrochloride extended-release tablets, USP (SR), are supplied for oral administration as 100 mg (blue), 150 mg (purple), and 200 mg (pink), film-coated, extended-release tablets. Each tablet contains the labeled amount of bupropion hydrochloride and the inactive ingredients: copovidone, cysteine hydrochloride,hypromellose, magnesium stearate, microcrystalline cellulose, polyethylene glycol,polysorbate 80 and titanium dioxide.In addition, the 100 mg tablet contains FD&C Blue No. 1 Brilliant Blue FCF Aluminium Lake, the 150 mg tablet contains FD&C Blue No. 2 Indigo Carmine Aluminium Lake and FD&C Red No. 40 Allura Red AC Aluminium Lake, and the 200 mg tablet contains FD&C Red No. 40 Allura Red AC Aluminium Lake. In addition, flavoring agent contains dextrose, ethyl alcohol, gum arabic, propylene glycol and silicon dioxide.

Bupropion hydrochloride extended-release tablets, USP (SR) meets USP Dissolution Test 2.

MEDICATION GUIDE
Bupropion Hydrochloride Extended-Release Tablets, USP (SR)
(bue proe' pee on hye'' droe klor' ide)
IMPORTANT: Be sure to read the three sections of this Medication Guide. The first section is about the risk of suicidal thoughts and actions with antidepressant medicines; the second section is about the risk of changes in thinking and behavior, depression and suicidal thoughts or actions with medicines used to quit smoking; and the third section is entitled “What Other Important Information Should I Know About bupropion hydrochloride extended-release tablets, (SR)?”
Antidepressant Medicines, Depression and Other Serious Mental Illnesses, and Suicidal Thoughts or Actions
This section of the Medication Guide is only about the risk of suicidal thoughts and actions with antidepressant medicines.
What is the most important information I should know about antidepressant medicines, depression and other serious mental illnesses, and suicidal thoughts or actions?
Antidepressant medicines may increase the risk of suicidal thoughts or actions in some children, teenagers, or young adults within the first few months of treatment.
Depression or other serious mental illnesses are the most important causes of suicidal thoughts and actions. Some people may have a particularly high risk of having suicidal thoughts or actions. These include people who have (or have a family history of) bipolar illness (also called manic- depressive illness) or suicidal thoughts or actions.
How can I watch for and try to prevent suicidal thoughts and actions in myself or a family member?
Pay close attention to any changes, especially sudden changes, in mood, behaviors, thoughts, or feelings. This is very important when an antidepressant medicine is started or when the dose is changed.
Call your healthcare provider right away to report new or sudden changes in mood, behavior, thoughts, or feelings.
Keep all follow-up visits with your healthcare provider as scheduled. Call the healthcare provider between visits as needed, especially if you have concerns about symptoms.
Call your healthcare provider right away if you or your family member has any of the following symptoms, especially if they are new, worse, or worry you:
• thoughts about suicide or dying • trouble sleeping (insomnia)
• attempts to commit suicide
• new or worse irritability
• new or worse depression • acting aggressive, being angry, or violent
• new or worse anxiety • acting on dangerous impulses
• feeling very agitated or restless • an extreme increase in activity and talking (mania)
• panic attacks • other unusual changes in behavior or mood
What else do I need to know about antidepressant medicines?
Never stop an antidepressant medicine without first talking to a healthcare provider. Stopping an antidepressant medicine suddenly can cause other symptoms.
Antidepressants are medicines used to treat depression and other illnesses. It is important to discuss all the risks of treating depression and also the risks of not treating it. Patients and their families or other caregivers should discuss all treatment choices with the healthcare provider, not just the use of antidepressants.
Antidepressant medicines have other side effects. Talk to the healthcare provider about the side effects of the medicine prescribed for you or your family member.
Antidepressant medicines can interact with other medicines. Know all of the medicines that you or your family member takes. Keep a list of all medicines to show the healthcare provider. Do not start new medicines without first checking with your healthcare provider.
It is not known if bupropion hydrochloride extended-release tablets (SR) are safe and effective in children under the age of 18.
Quitting Smoking, Quit-Smoking Medications, Changes in Thinking and Behavior, Depression, and Suicidal Thoughts or Actions
This section of the Medication Guide is only about the risk of changes in thinking and behavior, depression and suicidal thoughts or actions with drugs used to quit smoking.
Although bupropion hydrochloride extended-release tablets, (SR) is not a treatment for quitting smoking, it contains the same active ingredient (bupropion hydrochloride) as ZYBAN which is used to help patients quit smoking.
Talk to your healthcare provider or your family member’s healthcare provider about:
all risks and benefits of quit-smoking medicines
all treatment choices for quitting smoking
When you try to quit smoking, with or without bupropion you may have symptoms that may be due to nicotine withdrawal, including:
• urge to smoke • frustration • restlessness
• depressed mood • anger • decreased heart rate
• trouble sleeping • feeling anxious • increased appetite
• irritability • difficulty concentrating • weight gain
Some people have even experienced suicidal thoughts when trying to quit smoking without medication. Sometimes quitting smoking can lead to worsening of mental health problems that you already have, such as depression.
Some people have had serious side effect while taking bupropion to help them quit smoking, including: New or worse mental health problems, such as changes in behavior or thinking, aggression, hostility, agitation, depression, or suicidal thoughts or actions. Some people had these symptoms when they began taking bupropion, and others developed them after several weeks of treatment, or after stopping bupropion. These symptoms happened more often in people who had a history of mental health problems before taking bupropion than in people without a history of mental health problems.
Stop taking bupropion hydrochloride extended-release tablets, (SR) and call your healthcare provider right away if you, your family, or caregiver notice any of these symptoms. Work with your healthcare provider to decide whether you should continue to take bupropion hydrochloride extended-release tablets, (SR). In many people, these symptoms went away after stopping bupropion hydrochloride extended-release tablets, (SR), but in some people symptoms continued after stopping bupropion hydrochloride extended-release tablets, (SR). It is important for you to follow-up with your healthcare provider until your symptoms go away. Before taking bupropion hydrochloride extended-release tablets, (SR) tell your healthcare provider if you have ever had depression or other mental health problems. You should also tell your healthcare provider about any symptoms you had during other times you tried to quit smoking, with or without bupropion.
What Other Important Information Should I Know About bupropion hydrochloride extended-release tablets, (SR)?
Seizures: There is a chance of having a seizure (convulsion, fit) with bupropion hydrochloride extended-release tablets, (SR), especially in people:
with certain medical problems.
who take certain medicines.
The chance of having seizures increases with higher doses of bupropion hydrochloride extended-release tablets, (SR). For more information, see the sections “Who should not take bupropion hydrochloride extended-release tablets, (SR)?” and “What should I tell my healthcare provider before taking bupropion hydrochloride extended-release tablets, (SR)?” Tell your healthcare provider about all of your medical conditions and all the medicines you take. Do not take any other medicines while you are taking bupropion hydrochloride tablets, (SR) unless your healthcare provider has said it is okay to take them.
If you have a seizure while taking bupropion hydrochloride extended-release tablets, (SR), stop taking the tablets and call your healthcare provider right away. Do not take bupropion hydrochloride extended-release tablets, (SR) again if you have a seizure.
High blood pressure (hypertension). Some people get high blood pressure, that can be severe, while taking bupropion hydrochloride extended-release tablets, (SR). The chance of high blood pressure may be higher if you also use nicotine replacement therapy (such as a nicotine patch) to help you stop smoking (see the section of this Medication Guide called “How should I take bupropion hydrochloride extended-release tablets, (SR)?”).
Manic episodes. Some people may have periods of mania while taking bupropion hydrochloride extended-release tablets (SR), including:
Greatly increased energy
Severe trouble sleeping
Racing thoughts
Reckless behavior
Unusually grand ideas
Excessive happiness or irritability
Talking more or faster than usual
If you have any of the above symptoms of mania, call your healthcare provider.
Unusual thoughts or behaviors. Some patients have unusual thoughts or behaviors while taking bupropion hydrochloride extended-release tablets, (SR), including delusions (believe you are someone else), hallucinations (seeing or hearing things that are not there), paranoia (feeling that people are against you), or feeling confused. If this happens to you, call your healthcare provider.
Visual problems.
eye pain
changes in vision
swelling or redness in or around the eye
Only some people are at risk for these problems. You may want to undergo an eye examination to see if you are at risk and receive preventative treatment if you are.
Severe allergic reactions. Some people can have severe allergic reactions to bupropion hydrochloride extended-release tablets (SR). Stop taking bupropion hydrochloride extended-release tablets (SR) and call your healthcare provider right away if you get a rash, itching, hives, fever, swollen lymph glands, painful sores in the mouth or around the eyes, swelling of the lips or tongue, chest pain, or have trouble breathing. These could be signs of a serious allergic reaction.
What are bupropion hydrochloride extended-release tablets, (SR)?
Bupropion hydrochloride extended-release tablets, (SR) are a prescription medicine used to treat adults with a certain type of depression called major depressive disorder.
Who should not take bupropion hydrochloride extended-release tablets, (SR)?
Do not take bupropion hydrochloride extended-release tablets, (SR) if you:
have or had a seizure disorder or epilepsy.
have or had an eating disorder such as anorexia nervosa or bulimia.
are taking any other medicines that contain bupropion, including ZYBAN (used to help people stop smoking) WELLBUTRIN ®, WELLBUTRIN XL ®, APLENZIN ®, FORFIVO XL ®. Bupropion is the same active ingredient that is in bupropion hydrochloride extended-release tablets (SR).
drink a lot of alcohol and abruptly stop drinking, or use medicines called sedatives (these make you sleepy), benzodiazepines, or anti-seizure medicines, and you stop using them all of a sudden.
take a monoamine oxidase inhibitor (MAOI). Ask your healthcare provider or pharmacist if you are not sure if you take an MAOI, including the antibiotic linezolid.
do not take an MAOI within 2 weeks of stopping bupropion hydrochloride extended-release tablets, (SR) unless directed to do so by your healthcare provider.
do not start bupropion hydrochloride extended-release tablets, (SR) if you stopped taking an MAOI in the last 2 weeks unless directed to do so by your healthcare provider.
are allergic to the active ingredient in bupropion hydrochloride extended-release tablets, (SR), bupropion, or to any of the inactive ingredients. See the end of this Medication Guide for a complete list of ingredients in bupropion hydrochloride extended-release tablets, (SR).
What should I tell my healthcare provider before taking bupropion hydrochloride extended-release tablets, (SR)?
Tell your healthcare provider if you have ever had depression, suicidal thoughts or actions, or other mental health problems. See “Antidepressant Medicines, Depression and Other Serious Mental Illnesses, and Suicidal Thoughts or Actions.”
Tell your healthcare provider about your other medical conditions including if you:
have liver problems, especially cirrhosis of the liver.
have kidney problems.
have, or have had, an eating disorder, such as anorexia nervosa or bulimia.
have had a head injury.
have had a seizure (convulsion, fit).
have a tumor in your nervous system (brain or spine).
have had a heart attack, heart problems, or high blood pressure.
are a diabetic taking insulin or other medicines to control your blood sugar.
drink alcohol.
abuse prescription medicines or street drugs.
are pregnant or plan to become pregnant. Talk to your healthcare provider about the risk to your unborn baby if you take bupropion hydrochloride extended-release tablets, (SR) during pregnancy.
Tell your healthcare provider if you become pregnant or think you are pregnant during treatment with bupropion hydrochloride extended-release tablets, (SR).
If you become pregnant during treatment with bupropion hydrochloride extended-release tablets, (SR), talk to your healthcare provider about registering with the National Pregnancy Registry for Antidepressants. You can register by calling 1-844-405-6185.
are breastfeeding or plan to breastfeed during treatment with bupropion hydrochloride extended-release tablets, (SR). Bupropion hydrochloride passes into your milk. Talk to your healthcare provider about the best way to feed your baby during treatment with bupropion hydrochloride extended-release tablets, (SR).
Tell your healthcare provider about all the medicines you take, including prescription and over-the-counter medicines, vitamins, and herbal supplements. Many medicines increase your chances of having seizures or other serious side effects if you take them while you are taking bupropion hydrochloride extended-release tablets, (SR).
How should I take bupropion hydrochloride extended-release tablets, (SR)?
Take bupropion hydrochloride extended-release tablets, (SR) exactly as prescribed by your healthcare provider. Do not change your dose or stop taking bupropion hydrochloride extended-release tablets, (SR) without talking to your healthcare provider first.
Swallow bupropion hydrochloride extended-release tablets, (SR) whole. Do not chew, cut, or crush bupropion hydrochloride extended-release tablets, (SR). If you do, the medicine will be released into your body too quickly. If this happens you may be more likely to get side effects including seizures. Tell your healthcare provider if you cannot swallow tablets.
Bupropion hydrochloride extended-release tablets, (SR) tablets may have an odor. This is normal.
Take bupropion hydrochloride extended-release tablets, (SR) at the same time each day.
Take your doses of bupropion hydrochloride extended-release tablets, (SR) at least 8 hours apart.
You may take bupropion hydrochloride extended-release tablets, (SR) with or without food.
If you miss a dose, do not take an extra dose to make up for the dose you missed. Wait and take your next dose at the regular time. This is very important. Too much bupropion hydrochloride extended-release tablets, (SR) can increase your chance of having a seizure.
If you take too much bupropion hydrochloride extended-release tablets, (SR), or overdose, call your local emergency room or poison control center right away.
Do not take any other medicines while taking bupropion hydrochloride extended-release tablets, (SR) unless your healthcare provider has told you it is okay.
If you are taking bupropion hydrochloride extended-release tablets, (SR) for the treatment of major depressive disorder, it may take several weeks for you to feel that bupropion hydrochloride extended-release tablets, (SR) is working. Once you feel better, it is important to keep taking bupropion hydrochloride extended-release tablets, (SR) exactly as directed by your healthcare provider. Call your healthcare provider if you do not feel bupropion hydrochloride extended-release tablets, (SR) is working for you.
What should I avoid while taking bupropion hydrochloride extended-release tablets, (SR)?
Limit or avoid using alcohol during treatment with bupropion hydrochloride extended-release tablets, (SR). If you usually drink a lot of alcohol, talk with your healthcare provider before suddenly stopping. If you suddenly stop drinking alcohol, you may increase your chance of having seizures.
Do not drive a car or use heavy machinery until you know how bupropion hydrochloride extended-release tablets, (SR) affects you. Bupropion hydrochloride extended-release tablets, (SR) can affect your ability to do these things safely.
What are possible side effects of bupropion hydrochloride extended-release tablets, (SR)?
Bupropion hydrochloride extended-release tablets, (SR) can cause serious side effects. See the sections at the beginning of this Medication Guide for information about serious side effects of bupropion hydrochloride extended-release tablets.
The most common side effects of bupropion hydrochloride extended-release tablets, (SR) include
headache • dizziness
dry mouth • sore throat
nausea • constipation
trouble sleeping
If you have nausea, take your medicine with food. If you have trouble sleeping, do not take your medicine too close to bedtime.
Tell your healthcare provider right away about any side effects that bother you.
These are not all the possible side effects of bupropion hydrochloride extended-release tablets (SR). For more information, ask your healthcare provider or pharmacist.
Call your doctor for medical advice about side effects. You may report side effects to FDA at 1-800-FDA-1088.
You may also report side effects to ScieGen Pharmaceuticals, Inc. at 1-855-724-3436.
How should I store bupropion hydrochloride extended-release tablets, (SR)?
Store bupropion hydrochloride extended-release tablets, (SR) at room temperature between 20° and 25°C (68° to 77°F).
Keep bupropion hydrochloride extended-release tablets, (SR) dry and out of the light.
Keep bupropion hydrochloride extended-release tablets, (SR) and all medicines out of the reach of children.
General information about bupropion hydrochloride extended-release tablets, (SR).
Medicines are sometimes prescribed for purposes other than those listed in a Medication Guide. Do not use bupropion hydrochloride extended-release tablets, (SR) for a condition for which it was not prescribed. Do not give bupropion hydrochloride extended-release tablets, (SR) to other people, even if they have the same symptoms you have. It may harm them.
If you take a urine drug screening test, bupropion hydrochloride extended-release tablets, (SR) may make the test result positive for amphetamines. If you tell the person giving you the drug screening test that you are taking bupropion hydrochloride extended-release tablets, (SR), they can do a more specific drug screening test that should not have this problem.
This Medication Guide summarizes important information about bupropion hydrochloride extended-release tablets, (SR). If you would like more information, talk with your healthcare provider. You can ask your healthcare provider or pharmacist for information about bupropion hydrochloride extended-release tablets, (SR) that is written for healthcare professionals.
For more information about bupropion hydrochloride extended-release tablets, (SR), call ScieGen Pharmaceuticals, Inc. at 1-855-724-3436.
What are the ingredients in bupropion hydrochloride extended-release tablets, USP (SR)?
Active ingredient: bupropion hydrochloride USP.
Inactive ingredients: copovidone, cysteine hydrochloride, hypromellose, magnesium stearate, microcrystalline cellulose, polyethylene glycol, polysorbate 80 and titanium dioxide. In addition, the 100 mg tablet contains FD&C Blue No. 1 Brilliant Blue FCF Aluminium Lake, the 150 mg tablet contains FD&C Blue No. 2 Indigo Carmine Aluminium Lake and FD&C Red No. 40 Allura Red AC Aluminium Lake, and the 200 mg tablet contains FD&C Red No. 40 Allura Red AC Aluminium Lake. In addition, flavoring agent contains dextrose, ethyl alcohol, gum arabic, propylene glycol and silicon dioxide.
This Medication Guide has been approved by the U.S. Food and Drug Administration.
WELLBUTRIN, WELLBUTRIN XL, and ZYBAN are registered trademarks of the GSK group of companies. The other brands listed are the trademarks of their respective owners.
Rx Only
Manufactured by:
ScieGen Pharmaceuticals, Inc.
Hauppauge, NY 11788, USA
Rev: 3/2021